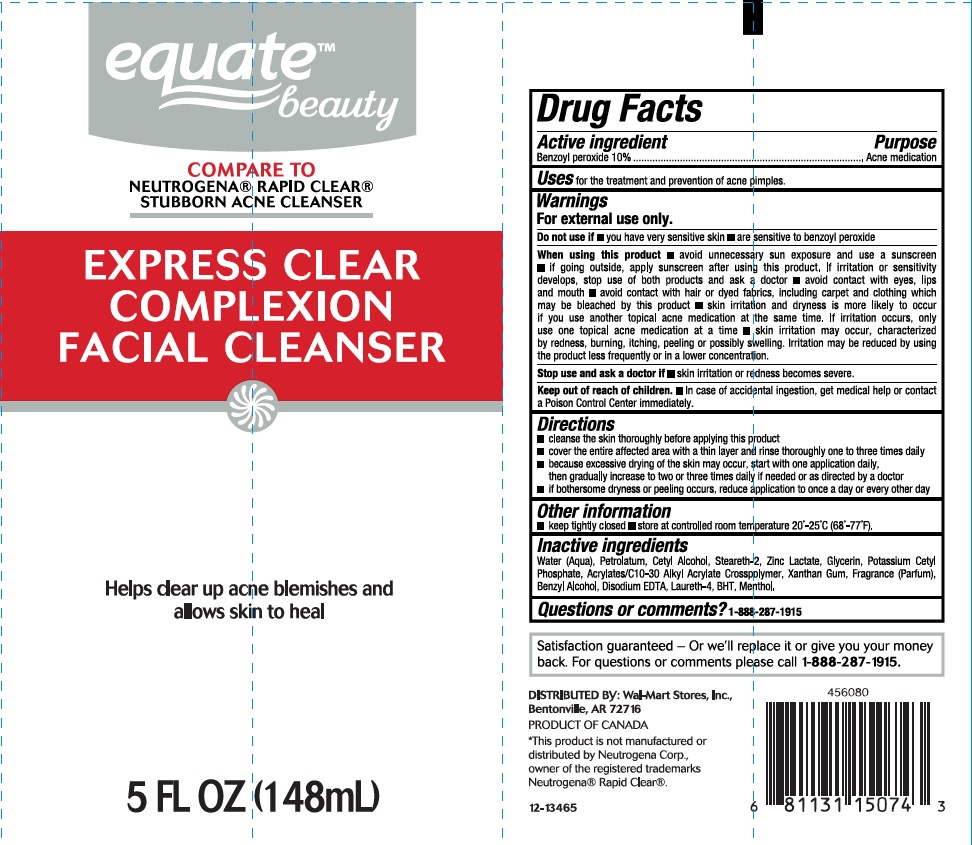 DRUG LABEL: Equate Clear Complexion Facial Cleanser
NDC: 49035-829 | Form: LIQUID
Manufacturer: Wal-mart Stores Inc
Category: otc | Type: HUMAN OTC DRUG LABEL
Date: 20161215

ACTIVE INGREDIENTS: BENZOYL PEROXIDE 100 mg/1 mL
INACTIVE INGREDIENTS: WATER; PETROLATUM; CETYL ALCOHOL; STEARETH-2; ZINC LACTATE; GLYCERIN; POTASSIUM CETYL PHOSPHATE; CARBOMER COPOLYMER TYPE A (ALLYL PENTAERYTHRITOL CROSSLINKED); XANTHAN GUM; BENZYL ALCOHOL; EDETATE DISODIUM; LAURETH-4; BUTYLATED HYDROXYTOLUENE; MENTHOL

Drug Facts

Active ingredient

Benzoyl Peroxide 10%

Purpose

Acne medication

Uses

for the treatment and prevention of acne pimples.

Warnings

For external use only.

Do not use if

- you have very sensitive skin
- are sensitive to benzoyl peroxide

When using this product

- avoid unnecessary sun exposure and use a sunscreen
- if going outside, apply sunscreen after using this product. If irritation or sensitivity develops, stop use of both products and ask a doctor
- avoid contact with eyes, lips and mouth
- avoid contact with hair or dyed fabrics, including carpet and clothing which may be bleached by this product
- skin irritation and dryness is more likely to occur if you use another topical acne medication at the same time. If irritation occurs, only use one topical acne medication at a time
- skin irritation may occur, characterized by redness, burning, itching, peeling or possibly swelling. Irritation may be reduced by using the product less frequently or in a lower concentration.

Stop use and ask a doctor if

- skin irritation or redness becomes severe.

Keep out of reach of children.

- In case of accidental ingestion, get medical help or contact a Poison Control Center immediately.

Directions

- cleanse the skin thoroughly before applying this product
- cover the entire affected area with a thin layer and rinse thoroughly one to three times daily
- because excessive drying of the skin may occur, start with one application daily, then gradually increase to two or three times daily if needed or as directed by a doctor
- if bothersome dryness or peeling occurs, reduce application to once a day or every other day.

Other information

- keep tightly closed
- store at controlled room temperature 20°C - 25°C (68°F - 77°F)

Inactive ingredients

Water (Aqua), Petrolatum, Cetyl Alcohol, Steareth-2, Zinc Lactate, Glycerin, Potassium Cetyl Phosphate, Acrylates/C10-30 Alkyl Acrylate Crosspolymer, Xanthan Gum, Fragrance (Parfum), Benzyl Alcohol, Disodium EDTA, Laureth-4, BHT, Menthol.

Questions or comments?

1-888-287-1915